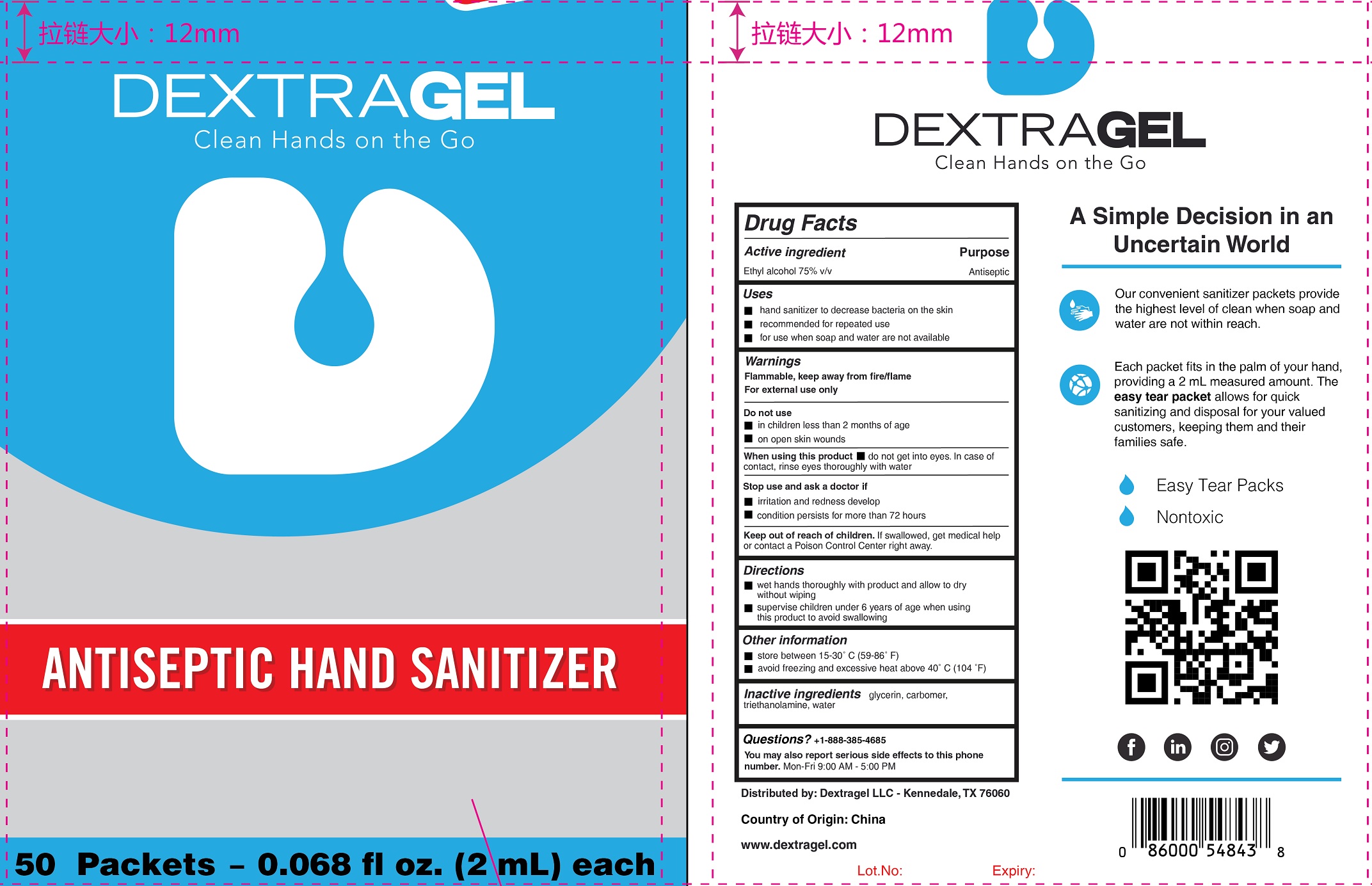 DRUG LABEL: Dextragel Antiseptic Hand Sanitizer
NDC: 71734-334 | Form: LIQUID
Manufacturer: JIANGMEN SHUIZIRUN SANITARY ARTICLES CO., LTD.
Category: otc | Type: HUMAN OTC DRUG LABEL
Date: 20201124

ACTIVE INGREDIENTS: ALCOHOL 75 mL/100 mL
INACTIVE INGREDIENTS: GLYCERIN; WATER; TROLAMINE

Active Ingredient

Ethly Alcohol 75%

Purpose

Antiseptic

USES:

- hand sanitizer to decrease bacteria on the skin
- recommended for repeated use
- for use when soap and water are not available

Warnings

For external use only.

Flammable. Keep away from fire/flame.

Do not use

- in children less than 2 months of age
- open skin wounds

When using this product

- do not get into eyes. in case of contat, rinse eyes thoroughly with water
- In case of contact with eyes,flush eyes thoroughly with water.

Stop use and ask a doctor if

- irritation and redness develop
- condition persists for more than 72 hours

Other information

- Store between 15-30℃ (59-68 ℉)
- Avoid freezing and excessive heat above 40℃ (104℉）

Keep out of reach of children. If swalllowed ,get medical help or contact poison Control right away.

Directions

- wet hand thoroughly with product and allow to dry without wiping
- supervise children under 6 years of age when using this product to avoid swallowing

Inactive Ingredients

Glycerine, Carbomer, Triethanolamine, Water